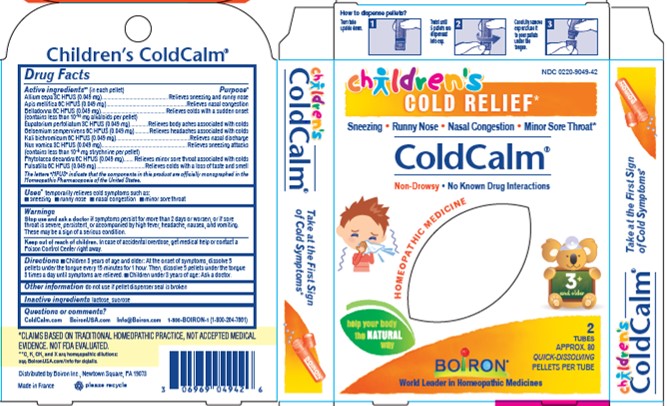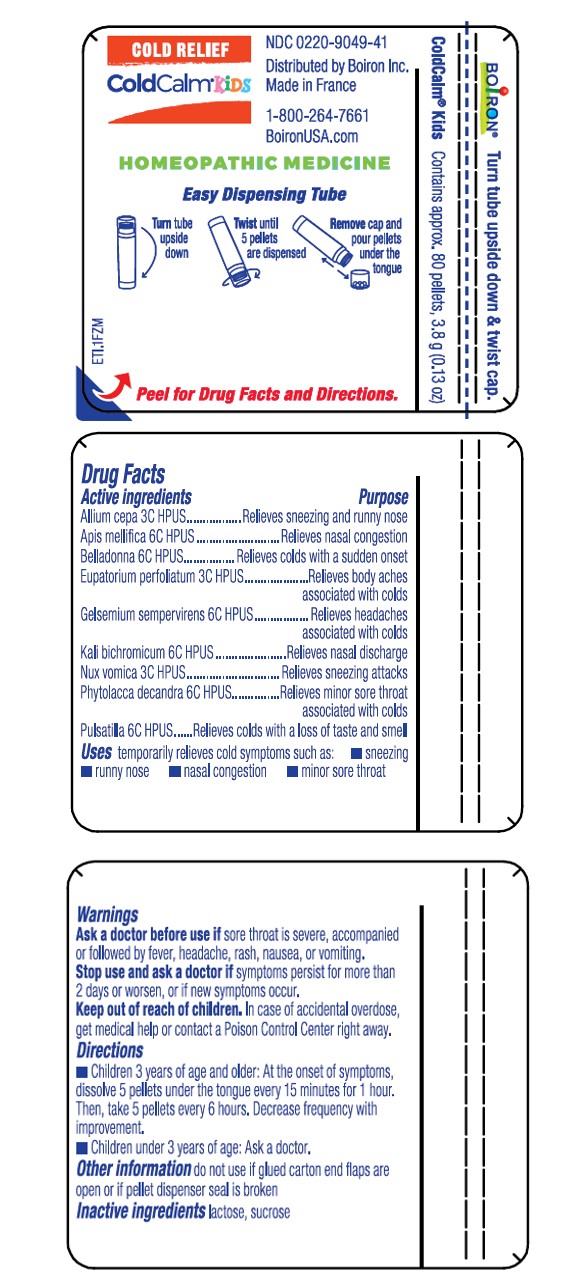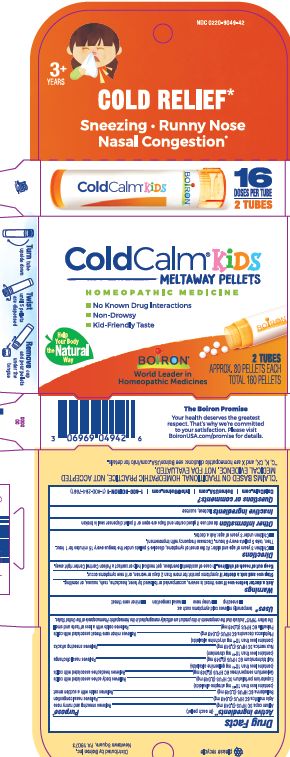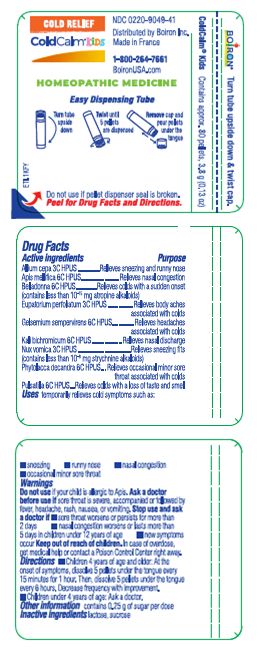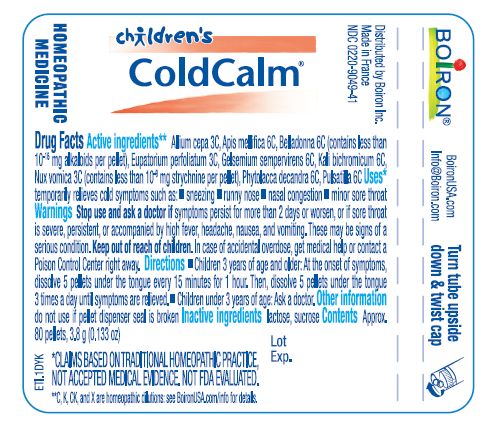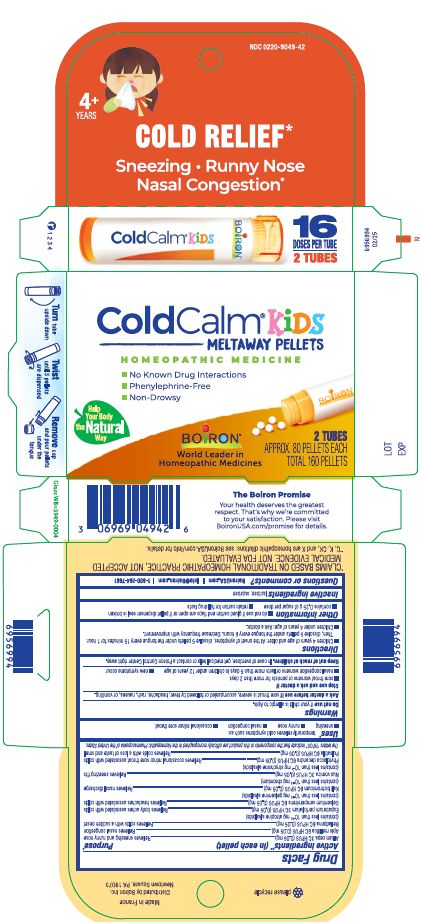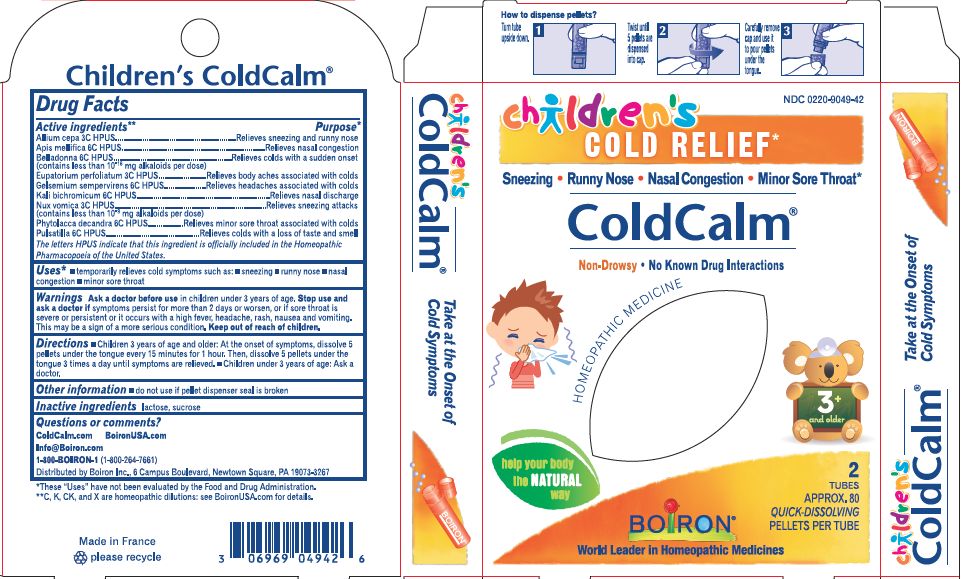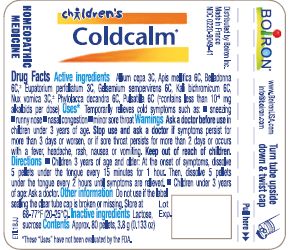 DRUG LABEL: Children Coldcalm
NDC: 0220-9049 | Form: PELLET
Manufacturer: Laboratoires Boiron
Category: homeopathic | Type: HUMAN OTC DRUG LABEL
Date: 20250331

ACTIVE INGREDIENTS: ONION 3 [hp_C]/1 1; APIS MELLIFERA 5 [hp_C]/1 1; ATROPA BELLADONNA 6 [hp_C]/1 1; EUPATORIUM PERFOLIATUM FLOWERING TOP 3 [hp_C]/1 1; GELSEMIUM SEMPERVIRENS ROOT 6 [hp_C]/1 1; POTASSIUM DICHROMATE 6 [hp_C]/1 1; STRYCHNOS NUX-VOMICA SEED 3 [hp_C]/1 1; PHYTOLACCA AMERICANA ROOT 6 [hp_C]/1 1; PULSATILLA VULGARIS 6 [hp_C]/1 1
INACTIVE INGREDIENTS: SUCROSE; LACTOSE

ColdCalm Kids

Active ingredients** (in each pellet)

Allium cepa 3C HPUS (0.05 mg)

Apis mellifica 6C HPUS (0.05 mg)

Belladonna 6C HPUS (0.05 mg)(contains less than 10^-15 mg atropine alkaloids)

Eupatorium perfoliatum 3C HPUS (0.05 mg)

Gelsemium sempervirens 6C HPUS (0.05 mg)(contains less than 10^-15 mg gelsemine alkaloids)

Kali bichromicum 6C HPUS (0.05 mg)(contains less than 10^-13 mg chromium)

Nux vomica 3C HPUS (0.05 mg)(contains less than 10^-8 mg strychnine alkaloids)

Phytolacca decandra 6C HPUS (0.05 mg)

Pulsatilla 6C HPUS (0.05 mg)

The letters "HPUS" indicate that the components in this product are officially monographed in the Homeopathic Pharmacopoeia of the United States.

Purpose*

Allium cepa 3C HPUS (0.05 mg)..........................................Relieves sneezing and runny nose

Apis mellifica 6C HPUS (0.05 mg)...................................................Relieves nasal congestion

Belladonna 6C HPUS (0.05 mg).......................................Relieves colds with a sudden onset

Eupatorium perfoliatum 3C HPUS (0.05 mg)…………..…Relieves body aches associated with colds

Gelsemium sempervirens 6C HPUS (0.05 mg)…….…......Relieves headaches associated with colds

Kali bichromicum 6C HPUS (0.05 mg)……………………..………………………….Relieves nasal discharge

Nux vomica 3C HPUS (0.05 mg)…………………………………………………………..Relieves sneezing fits

Phytolacca decandra 6C HPUS (0.05 mg)….Relieves occasional minor sore throat associated with colds

Pulsatilla 6C HPUS (0.05 mg)…..…………………..............Relieves colds with a loss of taste and smell

Uses*

temporarily relieves cold symptoms such as:

- sneezing
- runny nose
- nasal congestion
- occasional minor sore throat

Do not use if your child is allergic to Apis.

Ask a doctor before use if sore throat is severe, accompanied or followed by fever, headache, rash, nausea, or vomiting.

Stop use and ask a doctor if

▪ sore throat worsens or persists for more than 2 days

▪ nasal congestion worsens or lasts more than 5 days in children under 12 years of age

▪ new symptoms occur

Keep out of reach of children. In case of overdose, get medical help or contact a Poison Control Center right away.

DOSAGE AND ADMINISTRATION

▪ Children 4 years of age and older: At the onset of symptoms, dissolve 5 pellets under the tongue every 15 minutes for 1 hour. Then, dissolve 5 pellets under the tongue every 6 hours. Decrease frequency with improvement.

▪ Children under 4 years of age: Ask a doctor.

INACTIVE INGREDIENT

lactose, sucrose

QUESTIONS

BoironUSA.com

Info@Boiron.com

(1-800-264-7661)

Made in France

Distributed by Boiron Inc.

Newtown Square, PA 19073

do not use if glued carton end flaps are open or if pellet dispenser seal is broken

contains 0.25 g of sugar per dose

retain carton for full drug facts

Do not use if pellet dispenser seal is broken.

COLD RELIEF*

Sneezing · Runny Nose

Nasal Congestion*

No Known Drug Interactions

Phenylephrine-Free

Non-Drowsy

2 TUBES

APPROX. 80 PELLETS EACH

TOTAL 160 PELLETS

Turn tube upside down

Twist until 5 pellets are dispensed

Remove cap and pour pellets under the tongue

*CLAIMS BASED ON TRADITIONAL HOMEOPATHIC PRACTICE, NOT ACCEPTED MEDICAL EVIDENCE. NOT FDA EVALUATED.

**C, K, CK, and X are homeopathic dilutions: see BoironUSA.com/info for details.